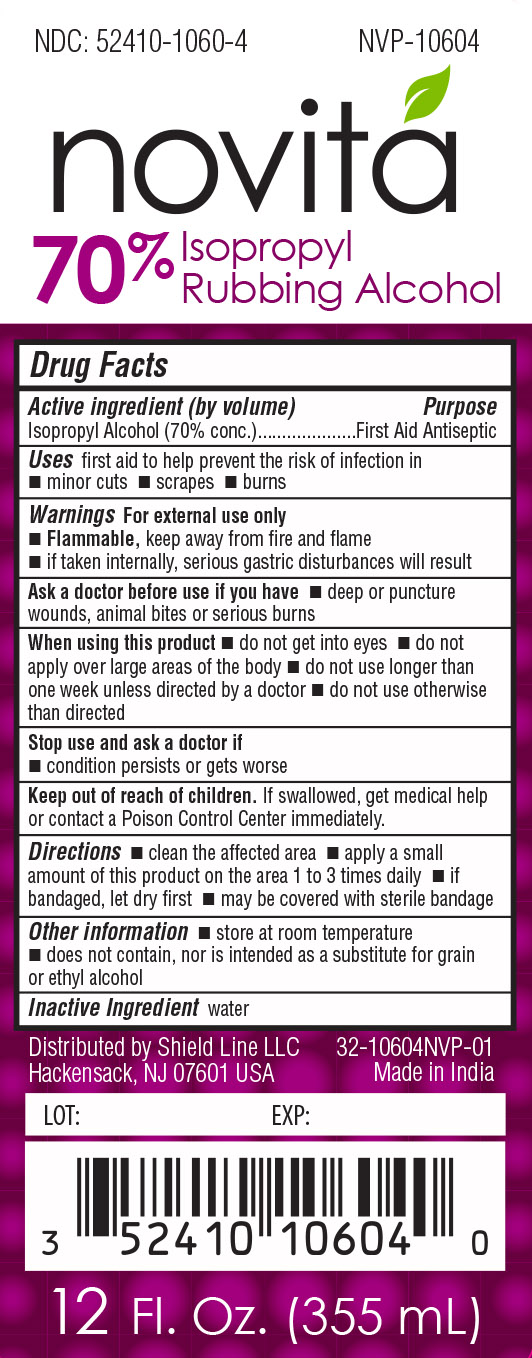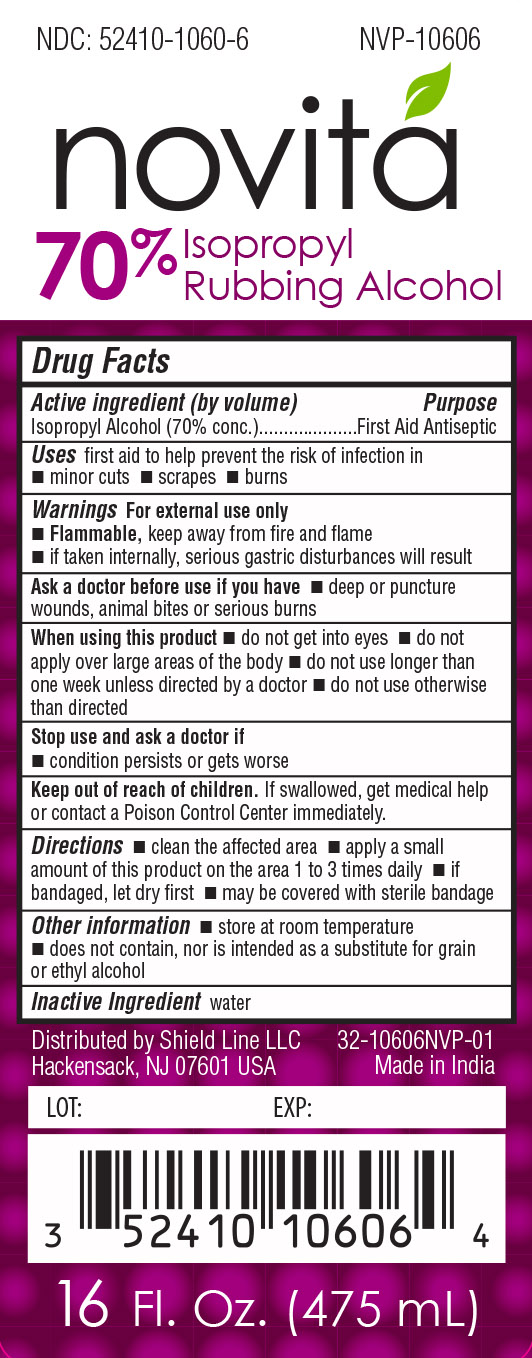 DRUG LABEL: NOVITA ISOPROPYL RUBBING ALCOHOL
NDC: 52410-1060 | Form: LIQUID
Manufacturer: Shield Line LLC
Category: otc | Type: HUMAN OTC DRUG LABEL
Date: 20210224

ACTIVE INGREDIENTS: ISOPROPYL ALCOHOL 70 mL/100 mL
INACTIVE INGREDIENTS: WATER

NOVITA ISOPROPYL ALCOHOL 70%

DRUG FACTS

Isopropyl Alcohol 70% (v/v)

Purpose

First Aid Antiseptic

Uses

first aid to prevent the risk of infection in

- minor cuts
- scrapes
- burns

Warnings

For external use only

- Flammable, Keep away from fire and flame
- if taken internally, serious gastric disturbances will result

Ask a doctor before use if you have

- deep or puncture wounds
- animal bites
- serious burns

When using this product

- do not get into eyes
- do not apply over large areas of body
- do not use longer than one week unless directed by a doctor
- do not use otherwise than directed

Stop use and ask a doctor if

- condition persists or gets worse

Keep out of reach of children

If swallowed, get medical table or contact a Poison Control Center immediately

Directions

- clean the affected area
- apply a small amount of this product on the area 1 to 3 times daily
- if bandaged, let dry first
- may be covered with a sterile bandage

Other information

- store at room temperature
- does not contain, nor is intended as substitute for grain or ethyl alcohol

Inactive Ingredient

water